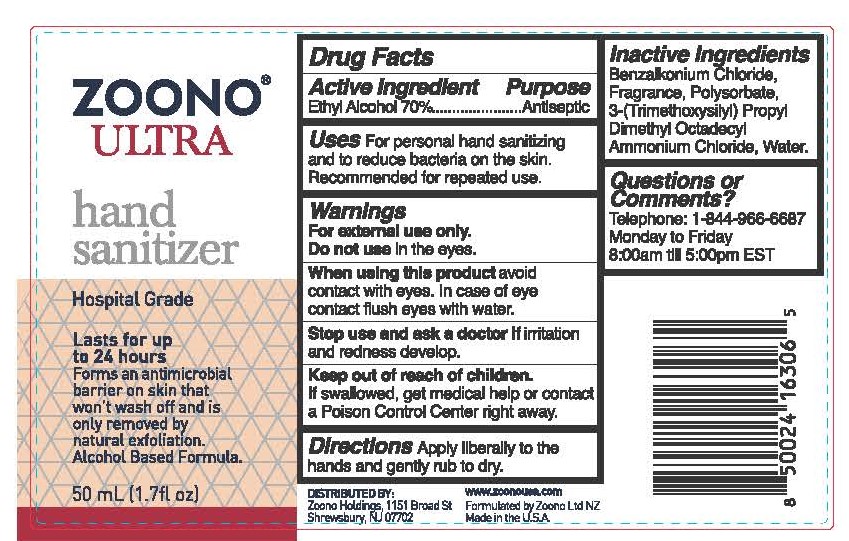 DRUG LABEL: Zoono Ultra Hand Sanitizer
NDC: 69221-501 | Form: LIQUID
Manufacturer: Zoono Holdings USA, LLC
Category: otc | Type: HUMAN OTC DRUG LABEL
Date: 20250828

ACTIVE INGREDIENTS: ALCOHOL 70 g/100 mL
INACTIVE INGREDIENTS: WATER

Zoono Ultra Hand Sanitizer

Active Ingredient

Ethyl Alchol 70%

Purpose

Antiseptic

Uses

For personal hand sanitizing and to reduce bacteria on the skin.

Recommended for repeated use.

Warnings

For external use only.

Do not use in the eyes.

When using this product

avoid contact with eyes. In case of eye contact flush eyes with water.

Stop use and ask a doctor if

irritation and redness develop.

Keep out of reach of children.

If swallowed get medical help or contact a Poison Control Cener right away.

Directions

Apply liberally to the hands and gently rub until dry.

Inactive Ingredients

Alcohol, Benzalkonium chloride, Fragrance, Polysorbate, Silica Complex 3-(Trimethoxysilyl) Propyl Dimethyl Octadecyl Ammonium Chloride, Water

Questions or Comments?

Telephone: 1-844-966-6687

Monday through Friday

8:00am till 5:00pm EST